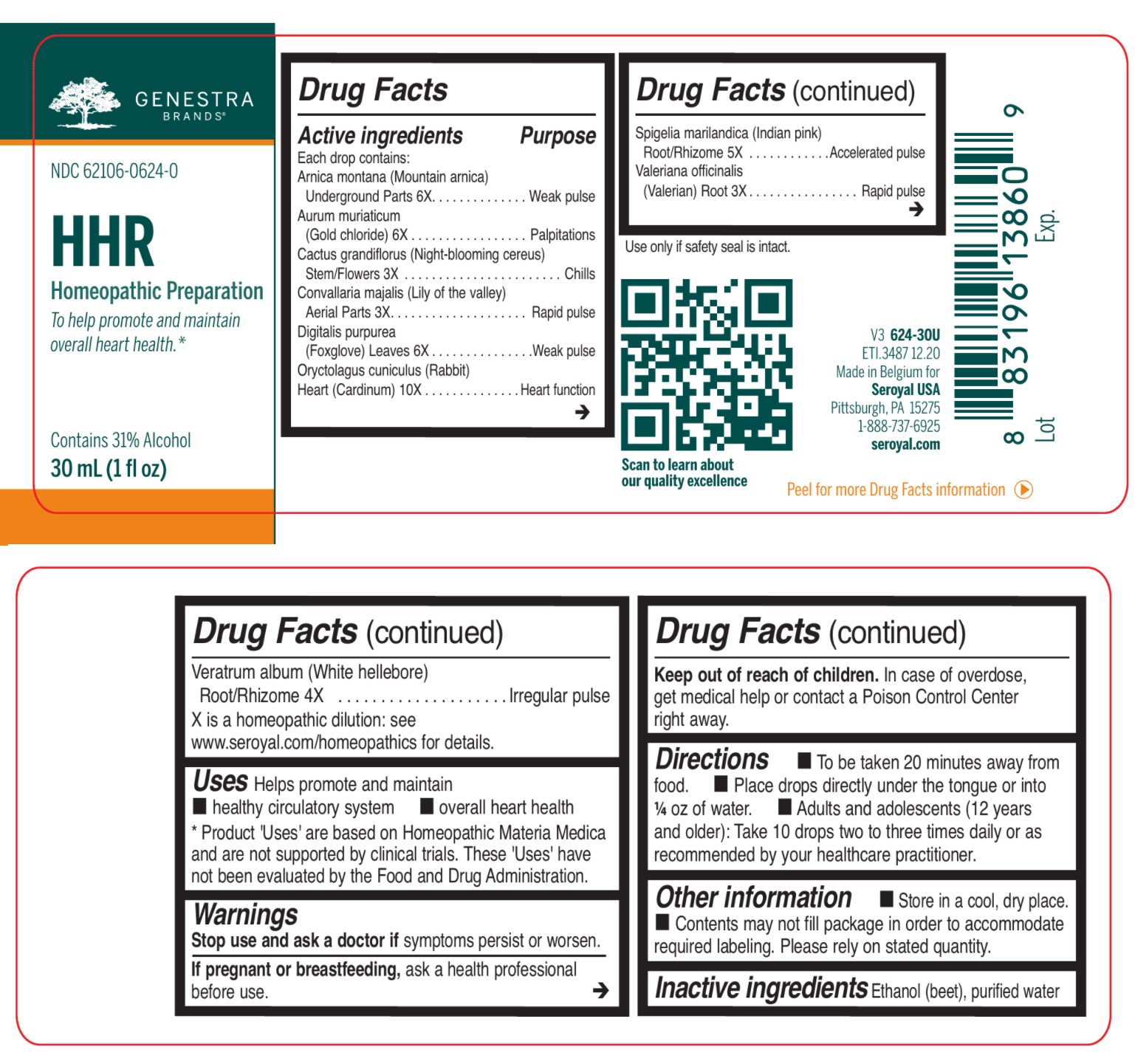 DRUG LABEL: HHR
NDC: 62106-0624 | Form: LIQUID
Manufacturer: Seroyal USA
Category: homeopathic | Type: HUMAN OTC DRUG LABEL
Date: 20210722

ACTIVE INGREDIENTS: GOLD TRICHLORIDE 6 [hp_X]/30 mL; SELENICEREUS GRANDIFLORUS STEM 3 [hp_X]/30 mL; CONVALLARIA MAJALIS 3 [hp_X]/30 mL; DIGITALIS 6 [hp_X]/30 mL; ORYCTOLAGUS CUNICULUS HEART 10 [hp_X]/30 mL; SPIGELIA MARILANDICA ROOT 5 [hp_X]/30 mL; VALERIAN 3 [hp_X]/30 mL; VERATRUM ALBUM ROOT 4 [hp_X]/30 mL; ARNICA MONTANA ROOT 6 [hp_X]/30 mL
INACTIVE INGREDIENTS: ALCOHOL; WATER

HHR

Active ingredients

Each drops contains:

Arnica montana (Mountain Arnica) Underground Parts 6X

Aurum muriaticum (Gold Chloride) 6X

Cactus grandiflorus (Night-Blooming cereus) Stem/Flowers 3X

Convallaria majalis (Lily of the valley) Aerial parts 3X

Digitalis purpurea (Foxglove) Leaves 6X

Oryctolagus cuniculus (Rabbit) heart (Cardinum) 10X

Spigelia marilandica (Indian pink) Root/Rhizome 5X

Valeriana officinalis (Valerian) Root 3X

Veratrum album (White hellebore) Root/Rhizome 4X

Uses

Helps promote and maintain a healthy circulatory system and overall heart health

Warnings:
Stop use and ask a doctor if symptoms persist or worsen.

If pregnant or breastfeeding, ask a health professional before use.
Keep out of reach of children.
In case of overdose, get medical help or contact a Poison Control Center right away.

Stop use and ask a doctor if symptoms persist or worsen.

PREGNANCY OR BREAST FEEDING

If pregnant or breastfeeding, ask a health professional before use.

Keep out of reach of children.

OVERDOSAGE

In case of overdose, get medical help or contact a Poison Control Center right away.

Inactive ingredients

Ethanol (beet), purified water

Other information

Store in a cool dry place.

Contents may not fill package in order to accommodate required labeling. Please rely on stated quantity.

Directions

To be taken 20 minutes away from food.

Place drops directly under the tongue or into 1/4 oz of water.

Adults and adolescents (12 years and older): Take 10 drops two to three times daily or as recommended by your healthcare practitioner.

Children (under 12 years): Take under the direction of your healthcare practitioner.

Uses

Helps promote and maintain a healthy circulatory system and overall heart health

Directions
To be taken 20 minutes away from food.
Place drops directly under the tongue or into 1/4 oz of water.
Adults and adolescents (12 years and older): Take 10 drops two to three times daily or as recommended by your healthcare practitioner.
Children (under 12 years): Take under the direction of your healthcare practitioner.

Use only if safety seal is intact.

PACKAGE LABEL

Genestra Brands

NDC 62106-0624-0

HHR

HOMEOPATHIC PREPRATION

To help promote and maintain overall heart health.

Contains 31% Alcohol

1 fl oz (30 mL)